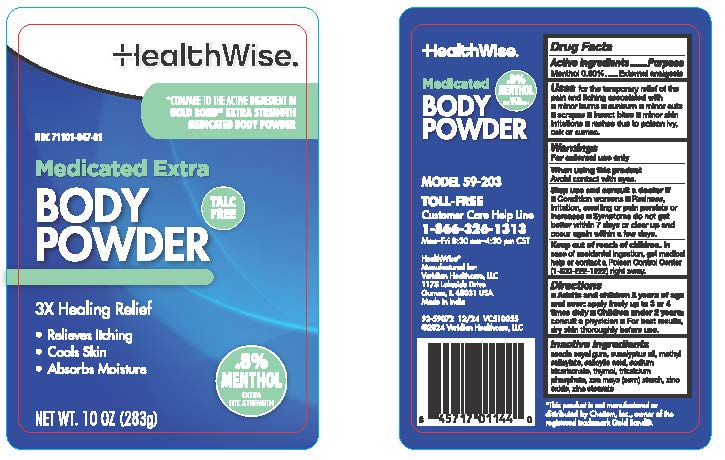 DRUG LABEL: HealthWise Medicated Extra Body Powder 10 oz
NDC: 71101-047 | Form: POWDER
Manufacturer: Veridian Healthcare
Category: otc | Type: HUMAN OTC DRUG LABEL
Date: 20241216

ACTIVE INGREDIENTS: MENTHOL 0.8 g/100 g
INACTIVE INGREDIENTS: ZINC STEARATE; SALICYLIC ACID; ACACIA; THYMOL; SODIUM BICARBONATE; TRICALCIUM PHOSPHATE; ZINC OXIDE; EUCALYPTUS OIL; STARCH, CORN; METHYL SALICYLATE

HealthWise Medicated Extra Body Powder 10 oz

Active Ingredient

Menthol 0.80%

Purpose

External analgesic

Uses

for the temporary relief of the pain and itch associated with:
■ minor cuts ■ scrapes ■ sunburn ■ insect bites ■ prickly heat ■ rashes ■ minor burns ■ minor skin irritation ■ dries the oozing of poison ivy, oak, and sumac.

Warnings

For external use only

When using this product

Avoid contact with eyes.

Stop use and consult a doctor if

■ Condition worsens ■ Redness, irritation, swelling or pain persists or increases ■ Symptoms do not get better within 7 days or clear up and occur again within a few days.

Keep out of reach of children

In case of accidental ingestion, get medical help or contact a Poison Control Center (1-800-222-1222) right away.

Directions

■ Adults and children 2 years of age and over: apply freely up to 3 or 4 times daily ■ Children under 2 years: consult a physician ■ For best results, dry skin thoroughly before use.

Inactive Ingredients

acacia seyal gum, eucalyptus oil, methyl salicylate, salicylic acid, sodium bicarbonate, thymol, tricalcium phosphate, zea mays (corn) starch, zinc oxide, zinc stearate

Questions or comments

Call toll-free 1-866-326-1313